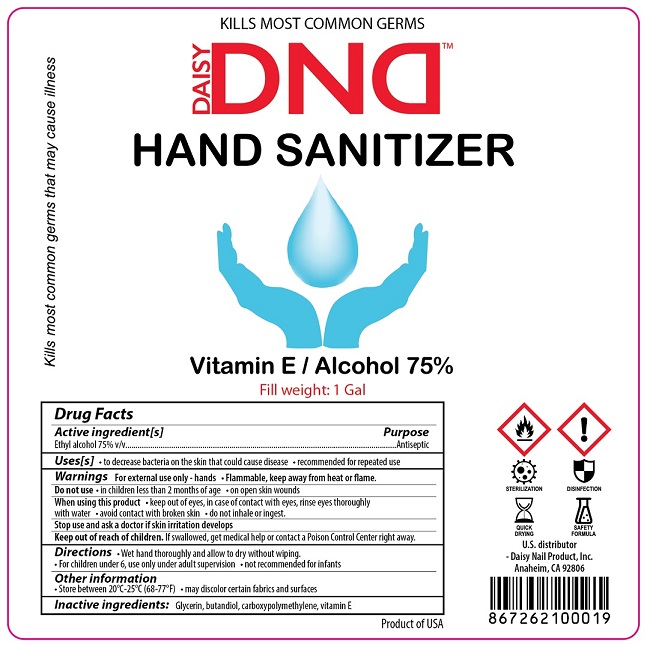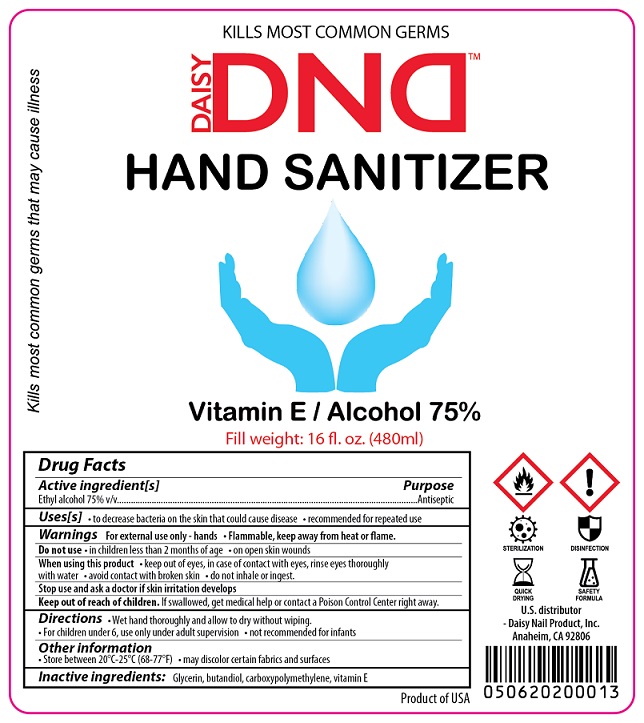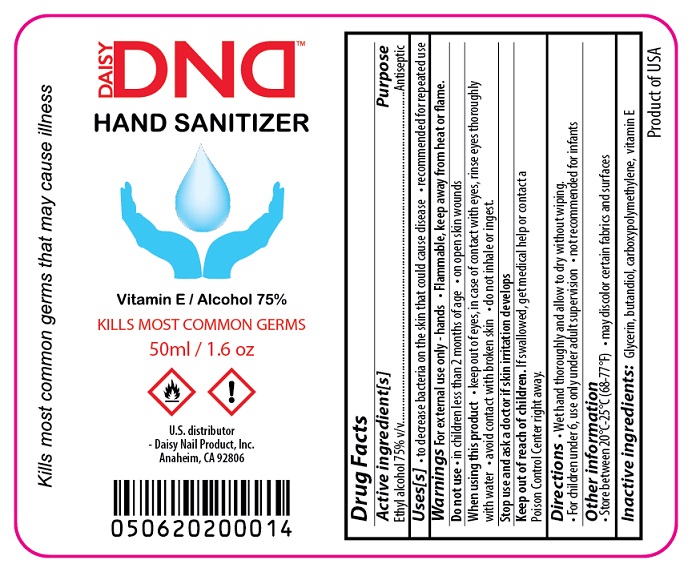 DRUG LABEL: Daisy DND
NDC: 78951-002 | Form: GEL
Manufacturer: Daisy Nail Product Inc.
Category: otc | Type: HUMAN OTC DRUG LABEL
Date: 20200610

ACTIVE INGREDIENTS: ALCOHOL 75 mL/100 mL
INACTIVE INGREDIENTS: GLYCERIN; BUTANEDIOL (MIXED ISOMERS); CARBOXYPOLYMETHYLENE; .ALPHA.-TOCOPHEROL

Active Ingredient

Ethyl Alcohol 75% v/v.

Purpose

Antiseptic

Use[s]

- to decrease bacteria on the skin that could cause disease
- recommended for repeated use

Warnings

For external use only- hands.
Flammable, keep away from heat or flame.
Do not use

- in children less than 2 months of age
- on open skin wounds

When using this product

- keep out of eyes, in case of contact with eyes, rinse eyes thoroughly with water.
- avoid contact with broken skin.
- do not inhale or ingest.

Stop use and ask a doctor if skin irritation develops.

Keep out of reach of children. If swallowed, get medical help or contact a Poison Control Center right away.

Directions

- Wet hand thoroughly and allow to dry without wiping.
- For children under 6, use only under adult supervision.
- Not recommended for infants.

Other information

- Store between 20°C-25°C (68-77°F).
- May discolor certain fabrics and surfaces.

Inactive ingredients

Glycerin, Bitandiol, Carboxypolymethylene, Vitamin E.